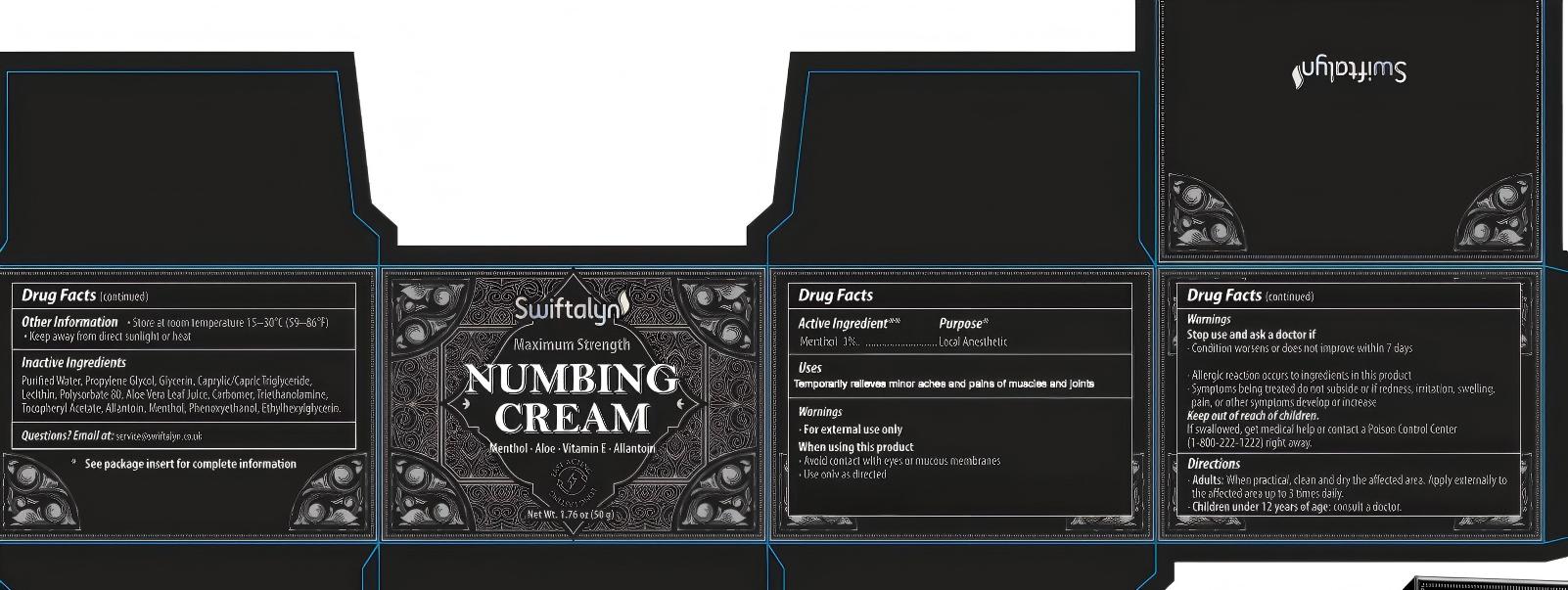 DRUG LABEL: Swiftalyn Numbing Cream
NDC: 87013-003 | Form: CREAM
Manufacturer: GENUINE INNOVATION LTD
Category: otc | Type: HUMAN OTC DRUG LABEL
Date: 20260219

ACTIVE INGREDIENTS: MENTHOL 1 mg/1 g
INACTIVE INGREDIENTS: PHENOXYETHANOL; ETHYLHEXYLGLYCERIN; PROPYLENE GLYCOL; ALOE VERA LEAF JUICE; TOCOPHEROL; CAPRYLIC/CAPRIC TRIGLYCERIDE; TRIETHANOLAMINE; ALLANTOIN; GLYCERIN; WATER; LECITHIN, SUNFLOWER; CARBOMER; POLYSORBATE 80

ACTIVE INGREDIENT

Menthol 1%

PURPOSE

Topical Analgesic

INDICATIONS AND USAGE

Temporary relief of minor aches and pains of muscles and joints

WARNINGS

For external use only ■ avoid contact with eyes or mucous membranes ■ Use only as directed ■ condition worsens or does not improve within 7 days ■ allergic reaction occurs to ingredients in this product ■ symptoms being treated do not subside or if redness, irritation, swelling, pain, or other symptoms develop or increase
If swallowed, get medical help or contact a Poison Control Center (1-800-222-1222) right away.

DOSAGE AND ADMINISTRATION

■ Adults: When practical, clean and dry the affected area. Apply externally to the affected area up to 3 times daily. ■ Children under 12 years of age: consult a doctor.

OTHER SAFETY INFORMATION

■ Store at room temperature 15–30°C (59–86°F) ■ Keep away from direct sunlight or heat

INACTIVE INGREDIENT

Water, Propylene Glycol, Glycerin, Caprylic/Capric Triglyceride, Lecithin, Polysorbate 80, Aloe Vera Leaf Juice, Carbomer, Triethanolamine, Tocopheryl Acetate, Allantoin, Menthol, Phenoxyethanol, Ethylhexylglycerin.

QUESTIONS

Email at: service@swiftalyn.co.uk

Keep out of reach of children